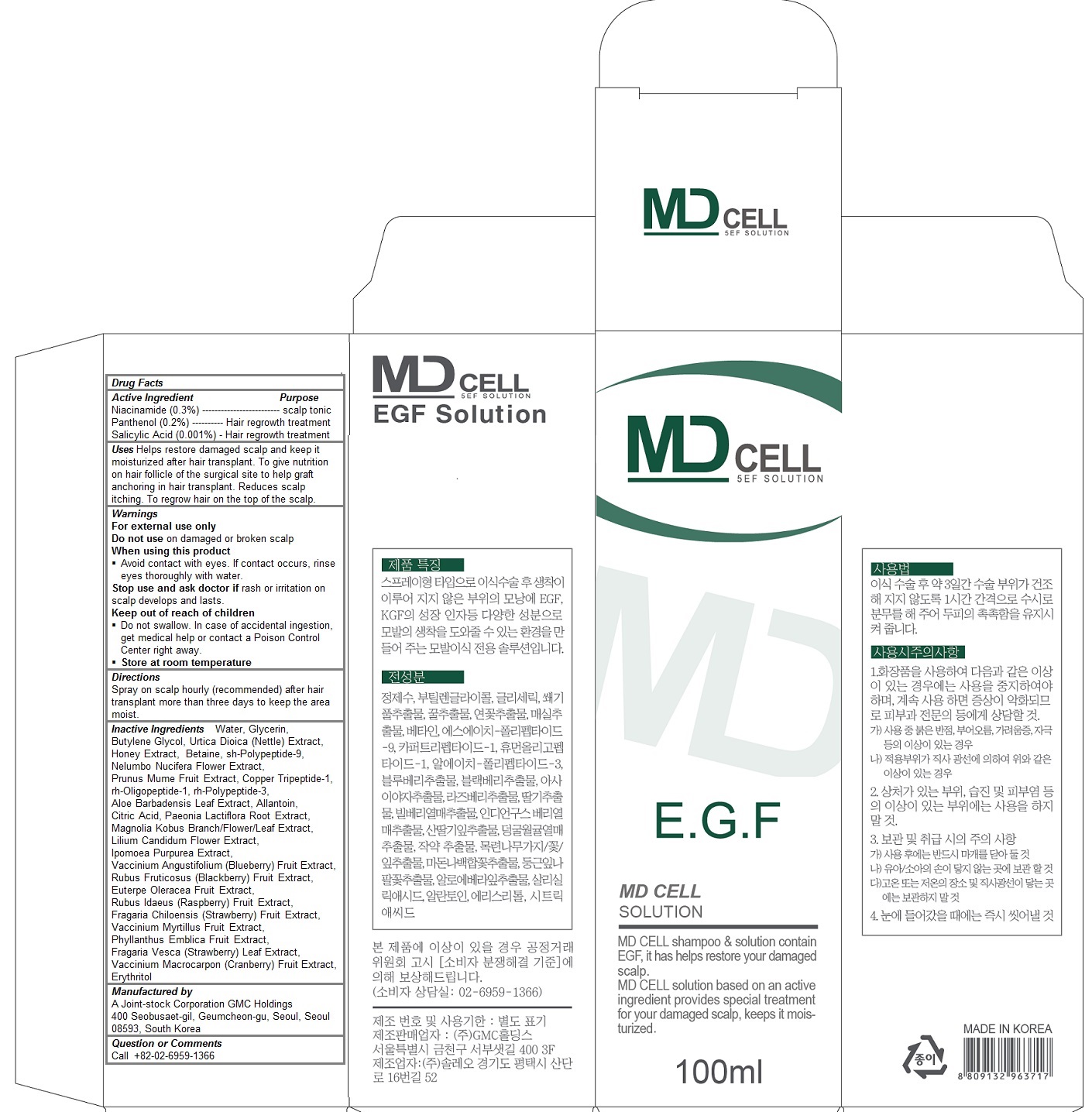 DRUG LABEL: MD CELL Solution
NDC: 70834-102 | Form: SPRAY
Manufacturer: A Joint-stock Corporation GMC Holdings
Category: otc | Type: HUMAN OTC DRUG LABEL
Date: 20160721

ACTIVE INGREDIENTS: Niacinamide 0.003 1/100 mL; Panthenol 0.002 1/100 mL; Salicylic Acid 0.00001 1/100 mL
INACTIVE INGREDIENTS: water; Glycerin; Butylene Glycol; URTICA DIOICA LEAF; HONEY; Betaine; NELUMBO NUCIFERA FLOWER; PRUNUS MUME FRUIT; PREZATIDE COPPER; NEPIDERMIN; FIBROBLAST GROWTH FACTOR 7; ALOE VERA LEAF; Allantoin; CITRIC ACID MONOHYDRATE; PAEONIA LACTIFLORA ROOT; MAGNOLIA KOBUS FLOWERING TOP; LILIUM CANDIDUM FLOWER; IPOMOEA PURPUREA TOP; LOWBUSH BLUEBERRY; BLACKBERRY; ACAI; RASPBERRY; BEACH STRAWBERRY; BILBERRY; PHYLLANTHUS EMBLICA FRUIT; FRAGARIA VESCA LEAF; CRANBERRY; Erythritol

MD CELL Solution

Active ingredients

Niacinamide (0.3%)

Panthenol (0.2%)

Salicylic Acid (0.001%)

Purpose

scalp tonic

hair regrowth treatment

Keep out of reach of children

- Do not swallow. In case of accidental ingestion, get medical help or contact a Poison Control Center right away.

Uses

Helps restore damaged scalp and keep it moisturized after hair transplant. To give nutrition on hair follicle of the surgical site to help graft anchoring in hair transplant. Reduces scalp itching. To regrow hair on the top of the scalp

Warnings

For external use only

Do not use on damaged or broken scalp

When using this product
- Avoid contact with eyes. If contact occurs, rinse eyes thoroughly with water.

Stop use and ask doctor if rash or irritation on scalp develops and lasts.

- Store at room temperature

Directions

Spray on scalp hourly (recommended) after hair transplant more than three days to keep the area moist.

Inactive Ingredients

Water, Glycerin, Butylene Glycol, Urtica Dioica (Nettle) Extract, Honey Extract, Betaine, sh-Polypeptide-9, Nelumbo Nucifera Flower Extract, Prunus Mume Fruit Extract, Copper Tripeptide-1, rh-Oligopeptide-1, rh-Polypeptide-3, Aloe Barbadensis Leaf Extract, Allantoin, Citric Acid, Paeonia Lactiflora Root Extract, Magnolia Kobus Branch/Flower/Leaf Extract, Lilium Candidum Flower Extract, Ipomoea Purpurea Extract, Vaccinium Angustifolium (Blueberry) Fruit Extract, Rubus Fruticosus (Blackberry) Fruit Extract, Euterpe Oleracea Fruit Extract, Rubus Idaeus (Raspberry) Fruit Extract, Fragaria Chiloensis (Strawberry) Fruit Extract, Vaccinium Myrtillus Fruit Extract, Phyllanthus Emblica Fruit Extract, Fragaria Vesca (Strawberry) Leaf Extract, Vaccinium Macrocarpon (Cranberry) Fruit Extract, Erythritol